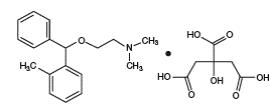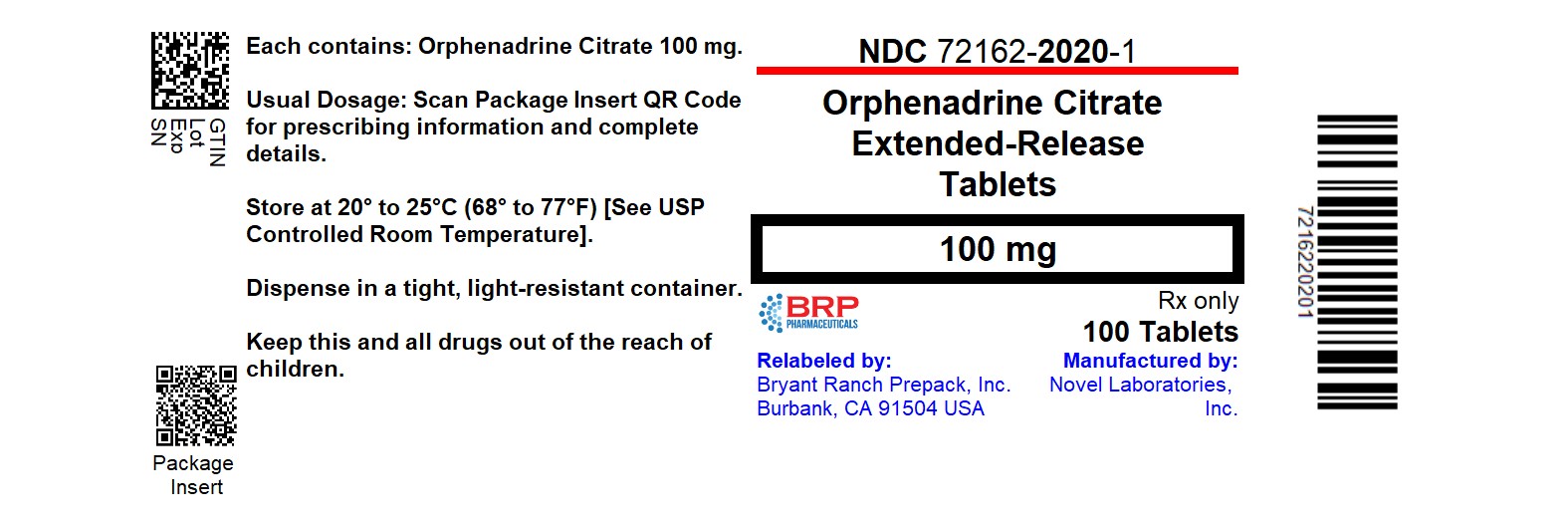 DRUG LABEL: ORPHENADRINE CITRATE
NDC: 72162-2020 | Form: TABLET, EXTENDED RELEASE
Manufacturer: Bryant Ranch Prepack
Category: prescription | Type: HUMAN PRESCRIPTION DRUG LABEL
Date: 20260226

ACTIVE INGREDIENTS: ORPHENADRINE CITRATE 100 mg/1 1
INACTIVE INGREDIENTS: HYPROMELLOSE, UNSPECIFIED; LACTOSE MONOHYDRATE; MAGNESIUM STEARATE

Orphenadrine Citrate Extended-Release Tablets
Rx Only

DESCRIPTION

Orphenadrine citrate is the citrate salt of orphenadrine. It occurs as a white, crystalline powder having a bitter taste. It is practically odorless; sparingly soluble in water, slightly soluble in alcohol. The chemical name of orphenadrine citrate is (±) -N,N-Dimethyl-2-[(o-methyl-α-phenylbenzyl)oxy]ethylamine citrate (1:1) having molecular formula C18H23NO•C6H8O7and molecular weight of 461.51. It has the following structural formula:

Each tablet for oral administration contains 100 mg orphenadrine citrate. Each Orphenadrine citrate extended- release tablet contains the following inactive ingredients: hydroxypropyl methylcellulose, lactose monohydrate and magnesium stearate.

CLINICAL PHARMACOLOGY

The mode of therapeutic action has not been clearly identified, but may be related to its analgesic properties. Orphenadrine citrate does not directly relax tense muscles in man. Orphenadrine citrate also possesses anti-cholinergic actions.

INDICATIONS AND USAGE

Orphenadrine citrate extended-release tablets are indicated as an adjunct to rest, physical therapy, and other measures for the relief of discomfort associated with acute painful musculoskeletal conditions.

CONTRAINDICATIONS

Orphenadrine citrate extended-release tablets are contraindicated in patients with glaucoma, pyloric or duodenal obstruction, stenosing peptic ulcers, prostatic hypertrophy or obstruction of the bladder neck, cardio-spasm (mega-esophagus) and myasthenia gravis. Orphenadrine citrate tablets are contraindicated in patients who have demonstrated a previous hypersensitivity to the drug.

WARNINGS

Some patients may experience transient episodes of light-headedness, dizziness or syncope. Orphenadrine may impair the ability of the patient to engage in potentially hazardous activities such as operating machinery or driving a motor vehicle; ambulatory patients should therefore be cautioned accordingly.

PRECAUTIONS

Confusion, anxiety and tremors have been reported in few patients receiving propoxyphene and orphenadrine concomitantly. As these symptoms may be simply due to an additive effect, reduction of dosage and/or discontinuation of one or both agents is recommended in such cases. Orphenadrine citrate should be used with caution in patients with tachycardia, cardiac decompensation, coronary insufficiency, cardiac arrhythmias.

Safety of continuous long-term therapy with orphenadrine has not been established. Therefore, if orphenadrine is prescribed for prolonged use, periodic monitoring of blood, urine and liver function values is recommended.

Pregnancy

Pregnancy Category C

Animal reproduction studies have not been conducted with orphenadrine. It is also not known whether orphenadrine can cause fetal harm when administered to a pregnant woman or can affect reproduction capacity. Orphenadrine should be given to a pregnant woman only if clearly needed.

Pediatric Use

Safety and effectiveness in pediatric patients have not been established.

ADVERSE REACTIONS

Adverse reactions of orphenadrine are mainly due to the mild anticholinergic action of orphenadrine, and are usually associated with higher dosage. Dryness of the mouth is usually the first adverse effect to appear. When the daily dose is increased, possible adverse effects include: tachycardia, palpitation, urinary hesitancy or retention, blurred vision, dilatation of pupils, increased ocular tension, weakness, nausea, vomiting, headache, dizziness, constipation, drowsiness, hypersensitivity reactions, pruritus, hallucinations, agitation, tremor, gastric irritation, and rarely urticaria and other dermatoses. Infrequently, an elderly patient may experience some degree of mental confusion.

These adverse reactions can usually be eliminated by reduction in dosage. Very rare cases of aplastic anemia associated with the use of orphenadrine tablets have been reported. No causal relationship has been established.

DRUG ABUSE AND DEPENDENCE

Orphenadrine has been chronically abused for its euphoric effects. The mood elevating effects may occur at therapeutic doses of orphenadrine.

OVERDOSAGE

Orphenadrine is toxic when overdosed and typically induces anticholinergic effects. In a review of orphenadrine toxicity, the minimum lethal dose was found to be 2 to 3 grams for adults; however, the range of toxicity is variable and unpredictable.

Treatment for orphenadrine overdose is evacuation of stomach contents (when necessary), charcoal at repeated doses, intensive monitoring, and appropriate supportive treatment of any emergent anticholinergic effects.

DOSAGE AND ADMINISTRATION

Adults

Two tablets per day; one in the morning and one in the evening.

HOW SUPPLIED

Orphenadrine citrate extended-release tablets 100 mg are round, white to off-white tablets, debossed NL4 on one side and plain on the other side and are supplied as:

- NDC 72162-2020-1 in bottles of 100 tablets
- NDC 72162-2020-5 in bottles of 500 tablets
- NDC 72162-2020-6 in bottles of 60 tablets

Store at 20°-25°C (68°-77°F) [see USP Controlled Room Temperature].

Dispense in a tight, light-resistant container.

Repackaged/Relabeled by:
Bryant Ranch Prepack
Burbank, CA 91504

PACKAGE LABEL

Orphenadrine Citrate 100 mg Tablets